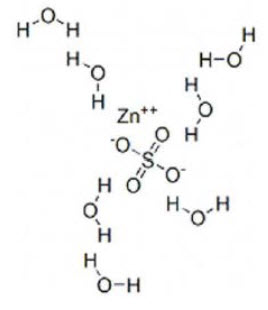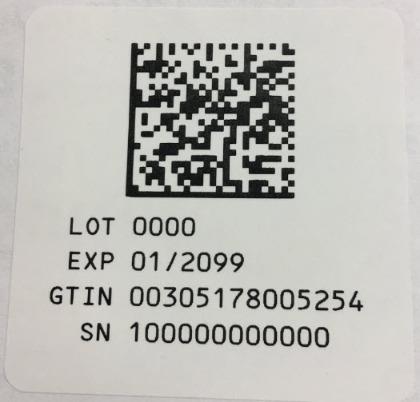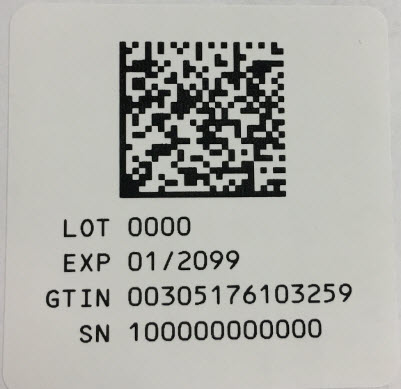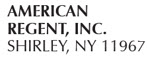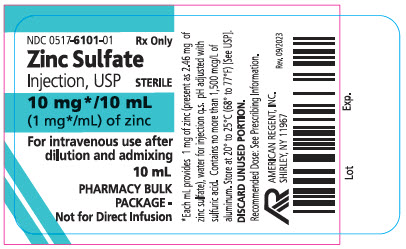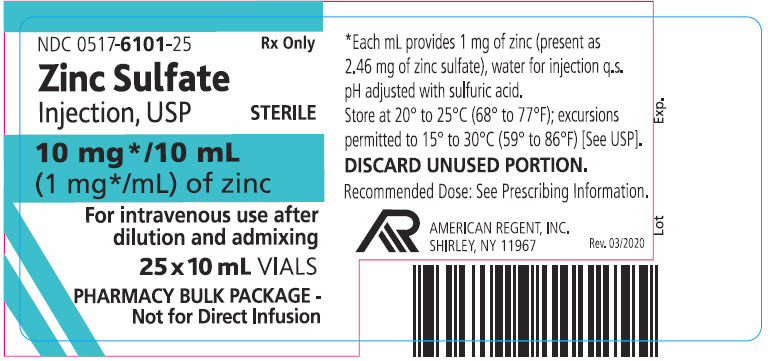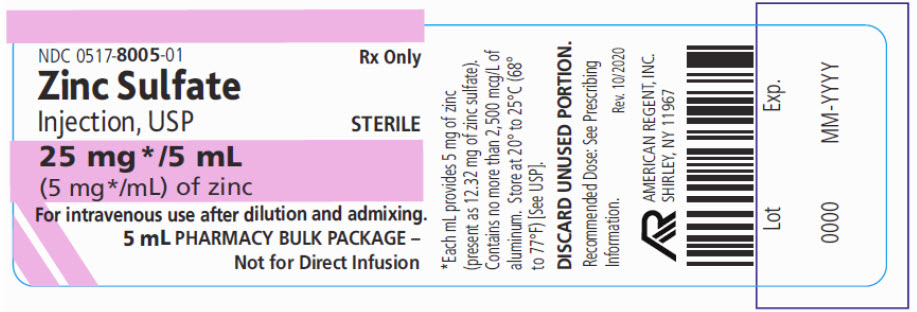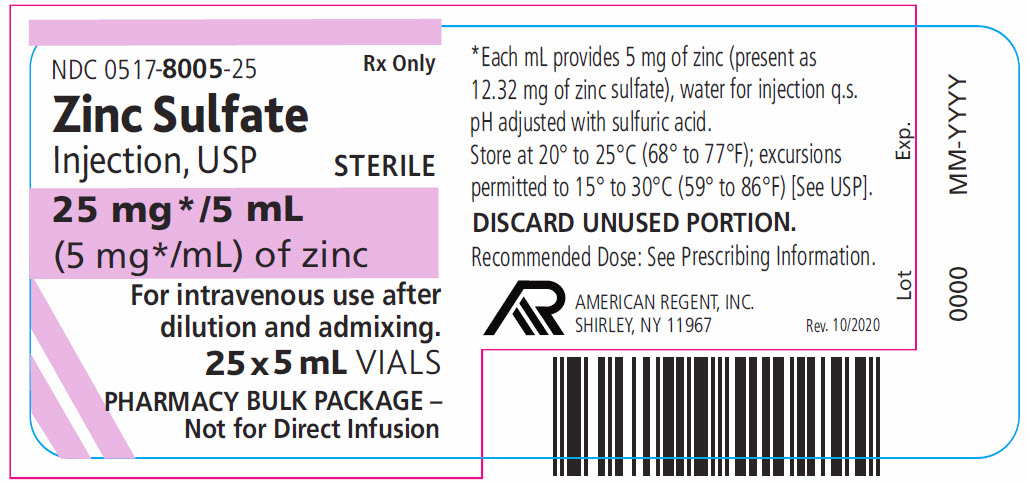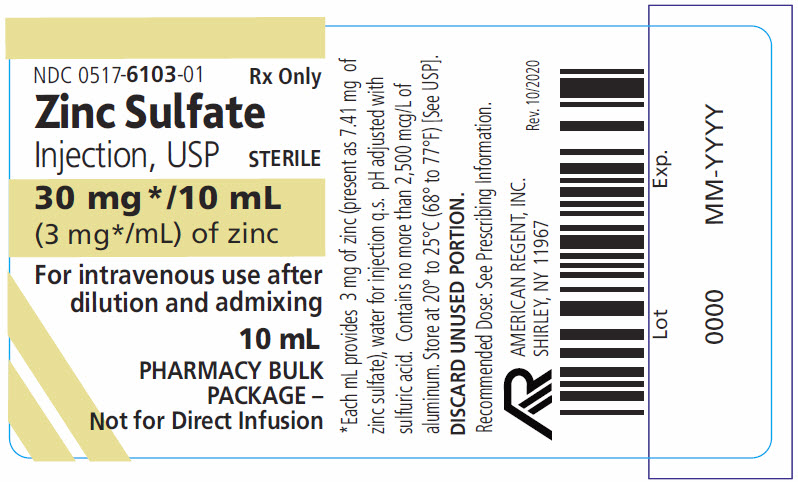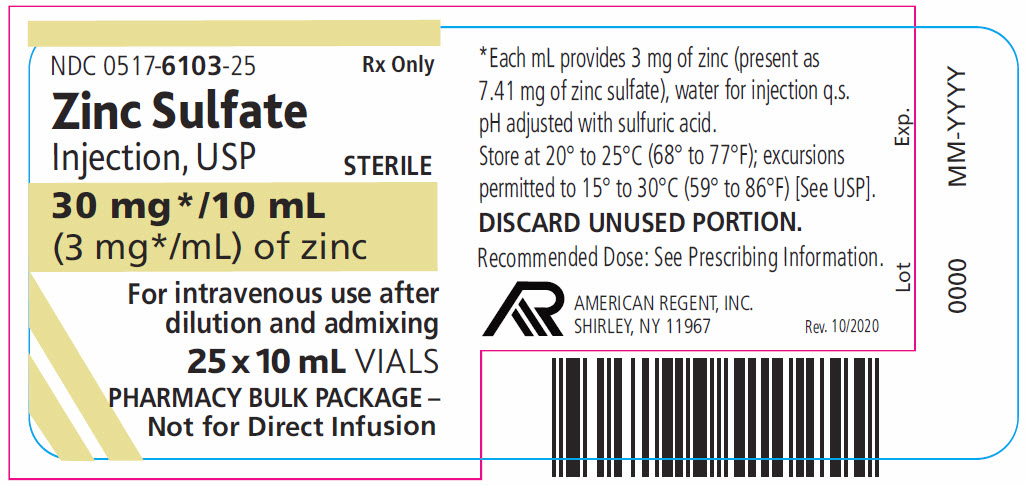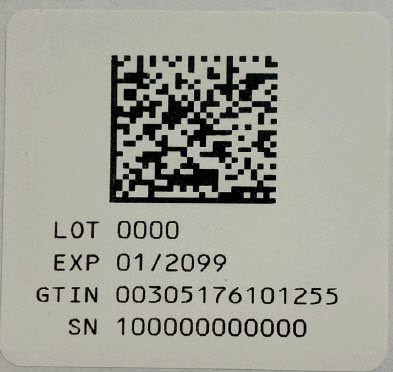 DRUG LABEL: Zinc Sulfate
NDC: 0517-6103 | Form: INJECTION, SOLUTION
Manufacturer: American Regent, Inc.
Category: prescription | Type: HUMAN PRESCRIPTION DRUG LABEL
Date: 20201001

ACTIVE INGREDIENTS: ZINC SULFATE 3 mg/1 mL
INACTIVE INGREDIENTS: WATER; SULFURIC ACID

HIGHLIGHTS OF PRESCRIBING INFORMATION

These highlights do not include all the information needed to use ZINC SULFATE INJECTION safely and effectively. See full prescribing information for ZINC SULFATE INJECTION.
ZINC SULFATE INJECTION, for intravenous use
Initial U.S. Approval: 1957

RECENT MAJOR CHANGES

Dosage and Administration
Preparation Instructions for Admixing Using a Parenteral Nutrition Container (2.3) 10/2020

Recommended Dosage and Monitoring in Adult and Pediatric Patients (2.5) 10/2020

1 INDICATIONS AND USAGE

Zinc Sulfate Injection is a trace element indicated in adult and pediatric patients as a source of zinc for parenteral nutrition when oral or enteral nutrition is not possible, insufficient, or contraindicated. (1)

2 DOSAGE AND ADMINISTRATION

- Pharmacy Bulk Package. Not for direct intravenous infusion. (2.1)
- See full prescribing information for information on preparation, administration, and general dosing considerations. (2.1, 2.2, 2.3, 2.4)

Recommended Dosage and Monitoring (2.5)

- Zinc Sulfate Injection provides 1 mg/mL, 3 mg/mL or 5 mg/mL of zinc.
- Zinc Sulfate Injection in a concentration of 1 mg/mL is recommended for use in pediatric patients, particularly those weighing less than 12 kg.
- Individualize the dosage based upon the patient’s clinical condition, nutritional requirements, and the contribution of oral or enteral zinc intake.
  o Adults: The recommended adult dosage is 3 mg/day for metabolically stable patients, with potential need for a higher daily dosage in monitored patients with small bowel fluid loss or excess stool or ileostomy output.
  o Pediatrics: The recommended dosage in pediatric patients is shown by age and estimated weight. The dosages in the table are general recommendations intended for most pediatric patients. However, based on clinical requirements, some patients may require a higher dosage.

Population | Estimated Weight for Age | Recommended Daily Dosage
Pediatric Patients | 10 kg and above | 50 mcg/kg; (up to 3 mg/day)
Pediatric Patients | 5 kg to less than 10 kg | 100 mcg/kg
Term Neonates | 3 kg to less than 5 kg | 250 mcg/kg*
Preterm Neonates | Less than 3 kg | 400 mcg/kg

*Term neonates have higher requirements in the first 3 months of life

- Monitor zinc concentrations and signs and symptoms of zinc deficiency, especially in pediatric patients, during treatment. Zinc concentrations may vary depending on the assay used and the laboratory reference range. The collection, processing, and storage of the blood samples for zinc analysis should be performed according to the laboratory’s sample requirements. Zinc concentrations in hemolyzed samples are falsely elevated due to release of zinc from erythrocytes. The lower end of the reported range in healthy adults in serum is 60 mcg/dL

3 DOSAGE FORMS AND STRENGTHS

Zinc Sulfate Injection, USP:

- 10 mg/10 mL (1 mg/mL) of zinc as a Pharmacy Bulk Package vial. (3)
- 30 mg/10 mL (3 mg/mL) of zinc as a Pharmacy Bulk Package vial. (3)
- 25 mg/5 mL (5 mg/mL) of zinc as a Pharmacy Bulk Package vial. (3)

4 CONTRAINDICATIONS

- Known hypersensitivity to zinc. (4, 5.6)

5 WARNINGS AND PRECAUTIONS

- Pulmonary Embolism due to Pulmonary Vascular Precipitates: If signs of pulmonary distress occur, stop the infusion and initiate a medical evaluation. (5.1)
- Vein Damage and Thrombosis: Solutions with osmolarity of 900 mOsmol/L or more must be infused through a central catheter. (2.1, 5.2)
- Aluminum Toxicity: Increase risk in patients with renal impairment, including preterm infants (5.3, 8.4)
- Monitoring and Laboratory Tests: Monitor fluid and electrolyte status, serum osmolarity, blood glucose, liver and kidney function, blood count and coagulation parameters throughout treatment. (5.4, 2.4)
- Copper Deficiency: If signs and symptoms develop, interrupt treatment with Zinc Sulfate Injection and check zinc, copper, and ceruloplasmin levels. (5.5)
- Hypersensitivity Reactions: If reactions occur, discontinue Zinc Sulfate Injection and initiate appropriate medical treatment. (5.6)

6 ADVERSE REACTIONS

No zinc-related adverse reactions in patients receiving intravenously administered parenteral nutrition solutions containing zinc within the recommended dosage range. (6)

To report SUSPECTED ADVERSE REACTIONS, contact American Regent, Inc. at 1-800-734-9236 or FDA at 1-800-FDA-1088 or www.fda.gov/medwatch.

FULL PRESCRIBING INFORMATION

RECENT MAJOR CHANGES

Dosage and Administration

Preparation Instructions for Admixing Using a Parenteral Nutrition Container (2.3)10/2020

Recommended Dosage and Monitoring in Adult and Pediatric Patients (2.5)10/2020

1 INDICATIONS AND USAGE

Zinc Sulfate Injection is indicated in adult and pediatric patients as a source of zinc for parenteral nutrition when oral or enteral nutrition is not possible, insufficient, or contraindicated.

2 DOSAGE AND ADMINISTRATION

2.1 Important Administration Information

Zinc Sulfate Injection is supplied as a pharmacy bulk package for admixing use only. It is not for direct intravenous infusion. Prior to administration, Zinc Sulfate Injection must be transferred to a separate parenteral nutrition container, diluted and used as an admixture in parenteral nutrition solutions.

The final parenteral nutrition solution is for intravenous infusion into a central or peripheral vein. The choice of a central or peripheral venous route should depend on the osmolarity of the final infusate. Solutions with osmolarity of 900 mOsmol/L or greater must be infused through a central catheter [see Warnings and Precautions (5.2)].

2.2 Preparation and Administration Instructions

- Zinc Sulfate Injection is not for direct intravenous infusion. Prior to administration, Zinc Sulfate Injection must be prepared and used as an admixture in parenteral nutrition solutions.
- Zinc Sulfate Injection is to be prepared only in a suitable work area such as a laminar flow hood (or an equivalent clean air compounding area). The key factor in the preparation is careful aseptic technique to avoid inadvertent touch contamination during mixing of solutions and addition of other nutrients.
- Visually inspect the diluted parenteral nutrition solution containing Zinc Sulfate Injection for particulate matter before admixing, after admixing, and prior to administration.

2.3 Preparation Instructions for Admixing Using a Parenteral Nutrition Container

- Inspect Zinc Sulfate Injection Bulk Pharmacy Package for particulate matter.
- Transfer Zinc Sulfate Injection to the parenteral nutrition container following the admixture of amino acids, dextrose, lipid emulsion (if added), and electrolytes solutions.
- Because additives may be incompatible, evaluate all additions to the parenteral nutrition container for compatibility and stability of the resulting preparation. Consult with pharmacist, if available. Questions about compatibility may be directed to American Regent. If it is deemed advisable to introduce additives to the parenteral nutrition container, use aseptic technique.
- Inspect the final parenteral nutrition solution containing Zinc Sulfate Injection to ensure that:
  - Precipitates have not formed during mixing or addition on additives.
  - The emulsion has not separated, if lipid emulsion has been added. Separation of the emulsion can be visibly identified by a yellowish streaking or the accumulation of yellowish droplets in the admixed emulsion.
  - Discard if any precipitates are observed.

Stability and Storage

- Penetrate vial closure only one time with a suitable sterile transfer device or dispensing set that allows measured dispensing of the contents.
- Use Zinc Sulfate Injection for admixing promptly once the sterile transfer set has been inserted into the Pharmacy Bulk Package container or not more than 4 hours at room temperature 20°C to 25°C (68°F to 77°F) (25ºC/77ºF) after the container closure has been penetrated. Discard any remaining drug.
- Use parenteral nutrition solutions containing Zinc Sulfate Injection promptly after mixing. Any storage of the admixture should be under refrigeration from 2ºC to 8ºC (36ºF to 46ºF) and limited to a period of time no longer than 9 days. After removal from refrigeration, use promptly and complete the infusion within 24 hours. Discard any remaining admixture.
- Protect the admixed parenteral nutrition solution from light.

2.4 Dosing Considerations

- The dosage of the final parenteral nutrition solution containing Zinc Sulfate Injection must be based on the concentrations of all components in the solution and the recommended daily nutritional requirements [see Dosage and Administration (2.5)]. Consult the prescribing information of all added components to determine the recommended nutritional requirements for dextrose and lipid emulsion, as applicable.
- Prior to administration of parenteral nutrition solution containing Zinc Sulfate Injection, correct severe fluid, electrolyte and acid-base disorders.

2.5 Recommended Dosage and Monitoring in Adult and Pediatric Patients

- Zinc Sulfate Injection provides 1 mg/mL, 3 mg/mL or 5 mg/mL of zinc.
- Zinc Sulfate Injection in a concentration of 1 mg/mL is recommended for use in pediatric patients, particularly those weighing less than 12 kg.
- The dosage of Zinc Sulfate Injection should be individualized based on the patient’s clinical condition, nutritional requirements, and the contribution of oral or enteral zinc intake.

Adults

The recommended adult dosage is 3 mg/day for metabolically stable patients, with potential need for a higher daily dosage in monitored patients with small bowel fluid loss or excess stool or ileostomy output.

Pediatric Patients

The recommended pediatric dosage is shown in Table 1 by age and estimated weight. The dosages in Table 1 are general recommendations intended for most pediatric patients. However, based on clinical requirements, some patients may require a higher dosage.

Table 1: Recommended Dosage of Zinc Sulfate Injection for Pediatric Patients by Age and Estimated Weight

Population | Estimated Weight for Age | Recommended Daily Dosage
Pediatric patients | 10 kg and above | 50 mcg/kg (up to 3 mg/day)
Pediatric patients | 5 kg to less than 10 kg | 100 mcg/kg
Term neonates | 3 kg to less than 5 kg | 250 mcg/kg*
Preterm neonates | Less than 3 kg | 400 mcg/kg

*Term neonates have higher requirements in the first 3 months of life
Monitoring

Monitor zinc concentrations during treatment. Also monitor patients clinically for signs and symptoms of zinc deficiency, especially in pediatrics. Zinc concentrations may vary depending on the assay used and the laboratory reference range. The collection, processing, and storage of the blood samples for zinc analysis should be performed according to the laboratory’s sample requirements. Zinc concentrations in hemolyzed samples are falsely elevated due to release of zinc from erythrocytes. The lower end of the reported range in healthy adults in serum is 60 mcg/dL

3 DOSAGE FORMS AND STRENGTHS

Zinc Sulfate Injection, USP:

- 10 mg/10 mL (1 mg/mL) of zinc as a clear, colorless solution in a 10 mL Pharmacy Bulk Package vial.
- 30 mg/10 mL (3 mg/mL) of zinc as a clear, colorless solution in a 10 mL Pharmacy Bulk Package vial.
- 25 mg/5 mL (5 mg/mL) of zinc as a clear, colorless solution in a 5 mL Pharmacy Bulk Package vial.

4 CONTRAINDICATIONS

Zinc Sulfate Injection is contraindicated in patients with known hypersensitivity to zinc [see Warnings and Precautions (5.6)]

5 WARNINGS AND PRECAUTIONS

5.1 Pulmonary Embolism due to Pulmonary Vascular Precipitates

Pulmonary vascular precipitates causing pulmonary vascular emboli and pulmonary distress have been reported in patients receiving parenteral nutrition. The cause of precipitate formation has not been determined in all cases; however, in some fatal cases, pulmonary emboli occurred as a result of calcium phosphate precipitates. Precipitation has occurred following passage through an in-line filter; in vivo precipitate formation may also have occurred. If signs of pulmonary distress occur, stop the parenteral nutrition infusion and initiate a medical evaluation. In addition to inspection of the solution [see Dosage and Administration (2.2, 2.3)], the infusion set and catheter should also periodically be checked for precipitates.

5.2 Vein Damage and Thrombosis

Zinc Sulfate Injection has a low pH and must be prepared and used as an admixture in parenteral nutrition solutions. It is not for direct intravenous infusion.

In addition, consider the osmolarity of the final parenteral nutrition solution in determining peripheral versus central administration. Solutions with an osmolarity of 900 mOsmol/L or greater must be infused through a central catheter [see Dosage and Administration (2.1)]. The infusion of hypertonic nutrient solutions into a peripheral vein may result in vein irritation, vein damage, and/or thrombosis. The primary complication of peripheral access is venous thrombophlebitis, which manifests as pain, erythema, tenderness or a palpable cord. Remove the catheter as soon as possible, if thrombophlebitis develops.

5.3 Aluminum Toxicity

Zinc Sulfate Injection contains aluminum that may be toxic.

Aluminum may reach toxic levels with prolonged parenteral administration if kidney function is impaired. Preterm infants are particularly at risk for aluminum toxicity because the kidneys are immature, and they require large amounts of calcium and phosphate solutions, which also contain aluminum.

Patients with impaired kidney function, including preterm infants, who receive greater than 4 to 5 mcg/kg/day of parenteral aluminum can accumulate aluminum at levels associated with central nervous system and bone toxicity. Tissue loading may occur at even lower rates of administration.

Exposure to aluminum from Zinc Sulfate Injection is not more than 0.6 mcg/kg/day. When prescribing Zinc Sulfate Injection for use in parenteral nutrition containing other small volume parenteral products, the total daily patient exposure to aluminum from the admixture should be considered and maintained at no more than 5 mcg/kg/day [see Use in Specific Populations (8.4)].

5.4 Monitoring and Laboratory Tests

Monitor zinc concentrations, fluid and electrolyte status, serum osmolarity, blood glucose, liver and kidney function, blood count and coagulation parameters throughout treatment [see Dosage and Administration (2.4)].

5.5 Copper Deficiency

Several post-marketing cases have reported that high doses of supplemental zinc (approximately 10 times the recommended dosage of 3 mg/day Zinc Sulfate Injection in adults) taken over extended periods of time (i.e., months to years) may result in decreased enteral copper absorption and copper deficiency. The cases reported the following complications of copper deficiency: anemia, leukopenia, thrombocytopenia, myeloneuropathy, and nephrotic-range proteinuria [see Adverse Reactions (6)].

If a patient develops signs and symptoms of copper deficiency during treatment with Zinc Sulfate Injection, interrupt zinc treatment and check zinc, copper, and ceruloplasmin levels. Copper deficiency should be treated with supplemental copper administration and discontinuation of zinc supplementation.

5.6 Hypersensitivity Reactions

Hypersensitivity reactions to subcutaneously administered zinc-containing insulin products were identified in postmarketing case reports. Reported reactions included injection site induration, erythema, pruritus, papular rash, generalized urticaria, facial swelling, and dyspnea. Patients did not manifest symptoms after changing to zinc-free insulin or another insulin product with a reduced amount of zinc. In some cases, allergy testing confirmed the allergy to the zinc component of the insulin product. If hypersensitivity reactions occur, discontinue Zinc Sulfate Injection and initiate appropriate medical treatment [see Contraindications (4)].

6 ADVERSE REACTIONS

No zinc-related adverse reactions have been reported in clinical studies or post-marketing reports in patients receiving intravenously administered parenteral nutrition solutions containing zinc sulfate within the recommended dosage range.

The following were identified in clinical studies or post-marketing reports. Because some of these reactions were reported voluntarily from a population of uncertain size, it is not always possible to reliably estimate their frequency or establish a causal relationship to drug exposure:

Adverse reactions with other components of parenteral nutrition solutions:

- Pulmonary embolism due to pulmonary vascular precipitates [see Warnings and Precautions (5.1)]
- Vein damage and thrombosis [see Warnings and Precautions (5.2)]
- Aluminum toxicity [see Warnings and Precautions (5.3)]

Adverse reactions with the use of zinc-containing products administered by other routes of administration:

- Copper deficiency [see Warnings and Precautions (5.5)]
- Hypersensitivity reactions [see Warnings and Precautions (5.6)]

8 USE IN SPECIFIC POPULATIONS

8.1 Pregnancy

Risk Summary

Administration of the approved recommended dose of Zinc Sulfate Injection in parenteral nutrition is not expected to cause major birth defects, miscarriage, or adverse maternal or fetal outcomes. Animal reproduction studies have not been conducted with intravenous zinc sulfate.

The estimated background risk of major birth defects and miscarriage for the indicated populations is unknown. All pregnancies have a background risk of birth defect, loss, or other adverse outcomes. In the U.S. general population, the estimated background risk of major birth defects and miscarriage in clinically recognized pregnancies is 2 to 4% and 15 to 20%, respectively.

Clinical Considerations

Disease-associated Maternal and/or Embryo-Fetal Risk

Deficiency of trace elements, including zinc, is associated with adverse pregnancy and fetal outcomes. Pregnant women have an increased metabolic demand for trace elements, including zinc. Parenteral nutrition with zinc should be considered if a pregnant woman’s nutritional requirements cannot be fulfilled by oral or enteral intake.

8.2 Lactation

Risk Summary

Zinc is present in human milk. Administration of the approved recommended dose of Zinc Sulfate Injection in parenteral nutrition is not expected to cause harm to a breastfed infant. There is no information on the effects of zinc sulfate on milk production. The developmental and health benefits of breastfeeding should be considered along with the mother’s clinical need for Zinc Sulfate Injection and any potential adverse effects on the breastfed infant from Zinc Sulfate Injection or from the underlying maternal condition.

8.4 Pediatric Use

Zinc Sulfate Injection is approved for use in the pediatric population, including neonates, as a source of zinc for parenteral nutrition when oral or enteral nutrition is not possible, insufficient, or contraindicated. Safety and dosing recommendations in pediatric patients are based on published literature describing controlled studies of zinc-containing products in pediatric patients [see Dosage and Administration (2.2)].

Because of immature renal function, preterm infants receiving prolonged parenteral nutrition treatment with Zinc Sulfate Injection may be at higher risk of aluminum toxicity [see Warnings and Precautions (5.3)].

8.5 Geriatric Use

Reported clinical experience with intravenous zinc sulfate has not identified a difference in zinc requirements between elderly and younger patients. In general, dose selection should be individualized based on the patient’s clinical condition, nutritional requirements, and additional nutritional intake provided orally or enterally to the patient.

10 OVERDOSAGE

There are reported cases of overdosage with intravenous zinc in parenteral nutrition:

- Seven adult patients received an inadvertent overdosage of 50 mg to 75 mg elemental zinc per day in parenteral nutrition solution for 26 to 60 days; 6 of the 7 patients developed hyperamylasemia (peak amylase values of 557 to 1850 Klein units; normal: 130 to 310). Amylase was not reported in one patient. Serum zinc concentrations ranged from 310 to 670 mcg/dL. None of the patients developed clinical signs of pancreatitis. Five of the 7 patients died of septic complications.
- One adult patient died of infectious complications after receiving an inadvertent overdosage of 7.4 grams of zinc sulfate (equivalent to 1.2 grams of elemental zinc per day for 2.5 days) in parenteral nutrition solution over 60 hours. The serum zinc concentration was 4184 mcg/dL. Symptoms of zinc overdosage also included hyperamylasemia, thrombocytopenia, anemia, vomiting and diarrhea.
- One preterm infant born at 26 weeks gestation died of cardiac failure following a medication error in which the parenteral nutrition solution contained 330 mg/100 mL instead of 330 mcg/100 mL of zinc sulfate (overdosage of 1000-fold)

Management

There is no known antidote for acute zinc toxicity. Management of zinc overdosage is supportive care based on presenting signs and symptoms.

11 DESCRIPTION

Zinc Sulfate Injection, USP is a sterile, non-pyrogenic, clear, colorless, and odorless solution intended for use as a trace element and an additive to intravenous solutions for parenteral nutrition.

10 mg/10 mL Pharmacy Bulk Package vial:
Each mL contains 1 mg of zinc present as a 2.46 mg of zinc sulfate and water for injection q.s.

30 mg/10 mL Pharmacy Bulk Package vial:
Each mL contains 3 mg of zinc present as 7.41 mg of zinc sulfate and Water for Injection q.s.

25 mg/5 mL Pharmacy Bulk Package vial:
Each mL contains 5 mg of zinc present as 12.32 mg of zinc sulfate and Water for Injection q.s.

All presentations do not contain preservatives.

The pH range is 2 to 4; pH may be adjusted with sulfuric acid.

1 mg/mL of Zinc Sulfate Injection contains no more than 1,500 mcg/L of aluminum and has a calculated osmolarity of 33 mOsmol/L.

3 mg/mL of Zinc Sulfate Injection contains no more than 2,500 mcg/L of aluminum and has a calculated osmolarity of 96.5 mOsmol/L.

5 mg/mL of Zinc Sulfate Injection contains no more than 2,500 mcg/L of aluminum and has a calculated osmolarity of 157.2 mOsmol/L.

Zinc sulfate heptahydrate has a molecular weight of 287.56 g/mol and a formula of ZnSO4·7H2O.

12 CLINICAL PHARMACOLOGY

12.1 Mechanism of Action

Zinc is an essential trace element. Zinc functions as a cofactor of various enzymes including DNA polymerases, RNA polymerases, alcohol dehydrogenase, and alkaline phosphatases. Zinc is a coordinator of protein structural folding, such as folding of “Zinc finger” motif that interacts with a variety of proteins, lipids, and nucleic acids. In addition, zinc is a catalyst of essential biochemical reactions, including activation of substrates of carbonic anhydrase in erythrocyte. Also, zinc is a signaling mediator modulating multiple signaling pathways.

12.2 Pharmacodynamics

Zinc sulfate exposure-response relationships and the time course of pharmacodynamic responses are unknown.

12.3 Pharmacokinetics

Distribution

Over 85% of total body zinc is found in skeletal muscle and bone. Other organs containing zinc are the liver, kidney, skin, brain, and heart. In blood, zinc is mainly localized within erythrocytes. Approximately 80% of serum zinc is bound to albumin and the remainder to alpha2-macroglobulin and amino acids.

Elimination

In adults, zinc is primarily excreted via the gastrointestinal tract and eliminated in the feces.

A smaller amount of zinc is excreted via the kidneys in the urine. Urinary zinc excretion rates in very low birth weight preterm infants are relatively high in the neonatal period, and they decline to a level on a body weight basis that is similar to that of normal adults by two months of age. Additionally, endogenous zinc loss occurs from hair, skin desquamation and sweat.

16 HOW SUPPLIED/STORAGE AND HANDLING

Zinc Sulfate Injection, USP is a clear, colorless solution supplied as:

- 10 mg/10 mL (1 mg/mL) of zinc in a 10 mL Pharmacy Bulk Package vial. Cartons of 25 vials (NDC 0517-6101-25)
- 30 mg/10 mL (3 mg/mL) of zinc in a 10 mL Pharmacy Bulk Package vial. Cartons of 25 vials (NDC 0517-6103-25)
- 25 mg/5 mL (5 mg/mL) of zinc in a 5 mL Pharmacy Bulk Package vial. Cartons of 25 vials (NDC 0517-8005-25)

Vial closure is not made with natural rubber latex.

Store at 20°C to 25°C (68°F to 77°F), excursions permitted to 15° to 30°C (59° to 86°F) [see USP Controlled Room Temperature].

For storage of admixed solution see Dosage and Administration (2.3).

17 PATIENT COUNSELING INFORMATION

Inform patients, caregivers or home healthcare providers of the following risks of Zinc Sulfate Injection:

- Pulmonary embolism due to pulmonary vascular precipitates [see Warnings and Precautions (5.1)]
- Vein damage and thrombosis [see Warnings and Precautions (5.2)]
- Aluminum toxicity [see Warnings and Precautions (5.3)]
- Copper deficiency [see Warnings and Precautions (5.5)]
- Hypersensitivity reactions [see Warnings and Precautions (5.6)]

IN8005
MG #46229

PRINCIPAL DISPLAY PANEL - 1 mg/mL Container Label

NDC 0517-6101-01

Rx Only

Zinc Sulfate Injection, USP

STERILE

10 mg*/10 mL
(1 mg*/mL) of zinc

For intravenous use after dilution and admixing.

10 mL PHARMACY BULK PACKAGE - Not for Direct Infusion

PRINCIPAL DISPLAY PANEL - 1 mg/mL Carton Labeling

NDC 0517-6101-25

Rx Only

Zinc Sulfate Injection, USP

STERILE

10 mg*/10 mL
(1 mg*/mL) of zinc

For intravenous use after dilution and admixing.

10 mL PHARMACY BULK PACKAGE - Not for Direct Infusion

NDC 0517-6103-01

Rx Only

Zinc Sulfate Injection, USP

STERILE

30 mg*/10 mL
(3 mg*/mL) of zinc

For intravenous use after dilution and admixing.

10 mL PHARMACY BULK PACKAGE

PRINCIPAL DISPLAY PANEL - 5 mL Container Label

NDC 0517-8005-01

Rx Only

Zinc Sulfate Injection, USP

STERILE

25 mg*/5 mL
(5 mg*/mL) of zinc

For intravenous use after dilution and admixing.

5 mL PHARMACY BULK PACKAGE - Not for Direct Infusion

PRINCIPAL DISPLAY PANEL - 5 mL Carton Labeling

NDC 0517-8005-25

Rx Only

Zinc Sulfate Injection, USP

STERILE

25 mg*/5 mL
(5 mg*/mL) of zinc

For intravenous use after dilution and admixing.

25 x 5 mL VIALS

PHARMACY BULK PACKAGE - Not for Direct Infusion

PRINCIPAL DISPLAY PANEL - 10 mL Container Label

NDC 0517-6103-01

Rx Only

Zinc Sulfate Injection, USP

STERILE

30 mg*/10 mL
(3 mg*/mL) of zinc

For intravenous use after dilution and admixing.

10 mL PHARMACY BULK PACKAGE - Not for Direct Infusion

PRINCIPAL DISPLAY PANEL - 10 mL Carton Labeling

NDC 0517-6103-25

Rx Only

Zinc Sulfate Injection, USP

STERILE

30 mg*/10 mL
(3 mg*/mL) of zinc

For intravenous use after dilution and admixing.

25 x 10 mL VIALS

PHARMACY BULK PACKAGE - Not for Direct Infusion